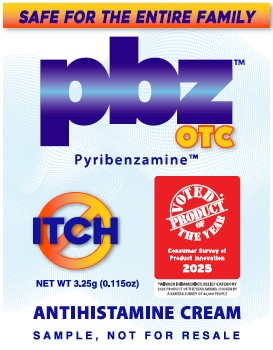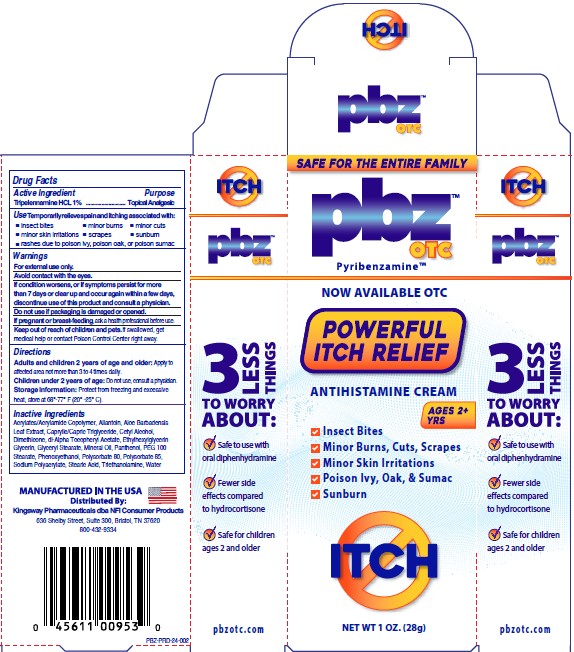 DRUG LABEL: PBZ OTC
NDC: 69993-151 | Form: CREAM
Manufacturer: Kingsway Pharmaceuticals dba NFI, LLC
Category: otc | Type: HUMAN OTC DRUG LABEL
Date: 20250829

ACTIVE INGREDIENTS: TRIPELENNAMINE 1 g/100 g
INACTIVE INGREDIENTS: ALLANTOIN; ALOE VERA LEAF; MEDIUM-CHAIN TRIGLYCERIDES; CETYL ALCOHOL; DIMETHICONE, UNSPECIFIED; .ALPHA.-TOCOPHEROL ACETATE, DL-; ETHYLHEXYLGLYCERIN; GLYCERIN; GLYCERYL MONOSTEARATE; MINERAL OIL; PANTHENOL; PEG-100 MONOSTEARATE; PHENOXYETHANOL; POLYSORBATE 80; POLYSORBATE 85; SODIUM POLYACRYLATE (8000 MW); STEARIC ACID; TROLAMINE; WATER

PBZ™ OTC Cream

Active Ingredient

Tripelennamine HCL 1%

Purpose

Topical Analgesic

Use

Temporarily relieves pain and itching associated with:

- insect bites
- minor burns
- minor cuts
- minor skin irritations
- scrapes
- sunburn
- rashes due to poison ivy, poison oak, or poison sumac

Warnings

For external use only.
Avoid contact with the eyes.
If condition worsens, or if symptoms persist for more than 7 days or clear up and occur again within a few days, discontinue use of this product and consult a physician.

Do not use

if packaging is damaged or opened.

If pregnant or breast-feeding,

ask a health professional before use

Keep out of reach of children and pets.

If swallowed, get medical help or contact Poison Control Center right away.

Directions

Adults and children 2 years of age and older: Apply to affected area not more than 3 to 4 times daily.
Children under 2 years of age: Do not use, consult a physician.
Storage Information: Protect from freezing and excessive heat, store at 68°-77°F (20°-25°C).

Inactive Ingredients

Acrylates/Acrylamide Copolymer, Allantoin, Aloe Barbadensis Leaf Extract, Caprylic/Capric Triglyceride, Cetyl Alcohol, Dimethicone, dl-Alpha Tocopheryl Acetate, Ethylhexylglycerin, Glycerin, Glyceryl Stearate, Mineral Oil, Panthenol, PEG 100 Stearate, Phenoxyethanol, Polysorbate 80, Polysorbate 85, Sodium Polyacrylate, Stearic Acid, Triethanolamine, Water

MANUFACTURED IN THE USA
Distributed By:
Kingsway Pharmaceuticals dba NFI Consumer Products
636 Shelby Street, Suite 300, Bristol, TN 37620
800-432-9334

PRINCIPAL DISPLAY PANEL – CARTON LABEL

SAFE FOR THE ENTRIE FAMILY
pbz™
OTC
Pyribenzamine™

NOW AVAILABLE OTC

POWERFUL
ITCH RELIEF

ANTIHISTAMINE CREAM
AGES 2+ YRS

✓ Insect Bites
✓ Minor Burns, Cuts, Scrapes
✓ Minor Skin Irritations
✓ Poison Ivy, Oak, & Sumac
✓ Sunburn

ITCH
Net WT 1 OZ. (28g)

PRINCIPAL DISPLAY PANEL – POUCH LABEL

SAFE FOR THE ENTRIE FAMILY
pbz™
OTC
Pyribenzamine™
ITCH
NET WT 3.25g (0.115oz)
VOTED
PRODUCT
of
THE YEAR

Consumer Survey of
Product Innovation
2025

*WINNER IN IMMEDIATE RELIEF CATEGORY
2025 PRODUCT OF THE YEAR AWARD, CHOSEN BY
A KANTAR SURVEY OF 40,000 PEOPLE
ANTIHISTAMINE CREAM
SAMPLE, NOT FOR RESALE